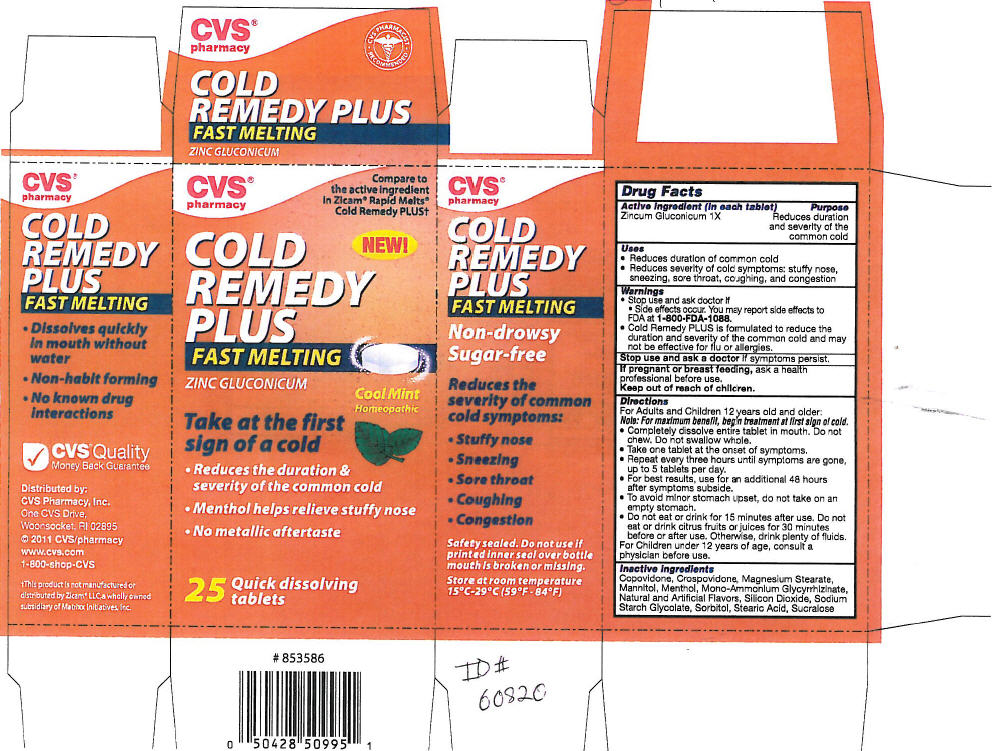 DRUG LABEL: NBE Cool Mint 
NDC: 64762-884 | Form: LOZENGE
Manufacturer: Dynamic Pharmaceuticals Inc.
Category: homeopathic | Type: HUMAN OTC DRUG LABEL
Date: 20110824

ACTIVE INGREDIENTS: ZINC GLUCONATE 1 [hp_X]/1 1
INACTIVE INGREDIENTS: Menthol; Copovidone K25-31; Crospovidone; Magnesium Stearate; Mannitol; Ammonium Glycyrrhizate; Silicon Dioxide; Sodium Starch Glycolate Type A Potato; Sorbitol; Stearic Acid; Sucralose

CVS®
pharmacy
COLD
REMEDY
PLUS
FAST MELTING

Drug Facts

Active Ingredient (in each tablet)

Zincum Gluconicum 1X

Purpose

Reduces duration and severity of the common cold

Uses

- Reduces duration of common cold
- Reduces severity of cold symptoms: stuffy nose, sneezing, sore throat, coughing, and congestion

Warnings

- Stop use and ask doctor if
  - Side effects occur. You may report side effects to FDA at 1-800-FDA-1088.
- Cold Remedy PLUS is formulated to reduce the duration and severity of the common cold and may not be effective for flu or allergies.

Stop use and ask a doctor if symptoms persist.

PREGNANCY OR BREAST FEEDING

If pregnant or breast feeding, ask a health professional before use.

Keep out of reach of children.

Directions

For Adults and Children 12 years old and older:

Note: For maximum benefit, begin treatment at first sign of cold.

- Completely dissolve entire tablet in mouth. Do not chew. Do not swallow whole.
- Take one tablet at the onset of symptoms.
- Repeat every three hours until symptoms are gone, up to 5 tablets per day.
- For best results, use for an additional 48 hours after symptoms subside.
- To avoid minor stomach upset, do not take on an empty stomach.
- Do not eat or drink for 15 minutes after use. Do not eat or drink citrus fruits or juices for 30 minutes before or after use. Otherwise, drink plenty of fluids.

For Children under 12 years of age, consult a physician before use.

Inactive Ingredients

Copovidone, Crospovidone, Magnesium Stearate, Mannitol, Menthol, Mono-Ammonium Glycyrrhizinate, Natural and Artificial Flavors, Silicon Dioxide, Sodium Starch Glycolate, Sorbitol, Stearic Acid, Sucralose

Distributed by:
CVS Pharmacy, Inc.
One CVS Drive,
Woonsocket, RI 02895

PRINCIPAL DISPLAY PANEL - 25 Tablet Bottle Carton

CVS®
pharmacy

Compare to
the active ingredient
in Zicam® Rapid Melts®
Cold Remedy PLUS†

NEW!

COLD
REMEDY
PLUS
FAST MELTING

ZINC GLUCONICUM

Cool Mint
Homeopathic

Take at the first
sign of a cold

- Reduces the duration &
  severity of the common cold
- Menthol helps relieve stuffy nose
- No metallic aftertaste

25
Quick dissolving
tablets